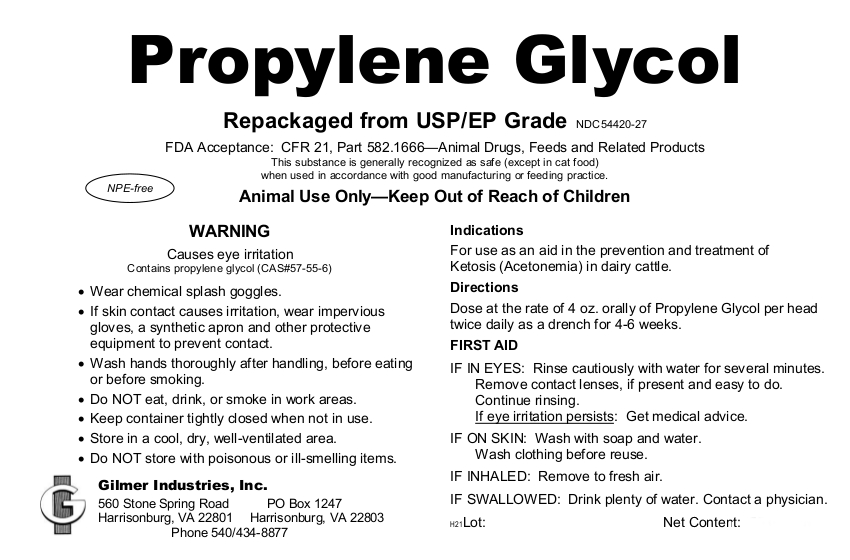 DRUG LABEL: Propylene Glycol
NDC: 54420-027 | Form: LIQUID
Manufacturer: Gilmer Industries, Inc.
Category: animal | Type: OTC ANIMAL DRUG LABEL
Date: 20210804

ACTIVE INGREDIENTS: PROPYLENE GLYCOL 0.00103698 g/1 L

Propylene Glycol

PURPOSE

For use as an aid in the prevention and treatment of Ketosis (Acetonemia) in dairy cattle.

Repackaged from USP/EP Grade

NPE-free

FDA Acceptance: CFR 21, Part 582.1666—Animal Drugs, Feeds and Related Products

This substance is generally recognized as safe (except in cat food) when used in accordance with good manufacturing or feeding practice.

USER SAFETY WARNINGS

Animal Use Only

Keep Out of Reach of Children

WARNING
Causes eye irritation

• Wear chemical splash goggles.

• If skin contact causes irritation, wear impervious gloves, a synthetic apron and other protective equipment to prevent contact.

• Wash hands thoroughly after handling, before eating or before smoking.

• Do NOT eat, drink, or smoke in work areas.

• Keep container tightly closed when not in use.

• Store in a cool, dry, well-ventilated area.

• Do NOT store with poisonous or ill-smelling items.

FIRST AID

IF IN EYES: Rinse cautiously with water for several minutes. Remove contact lenses, if present and easy to do. Continue rinsing.
If eye irritation persists: Get medical advice.

IF ON SKIN: Wash with soap and water. Wash clothing before reuse.

IF INHALED: Remove to fresh air.

IF SWALLOWED: Drink plenty of water. Contact a physician.

Directions

Dose at the rate of 4 oz. orally of Propylene Glycol per head twice daily as a drench for 4-6 weeks.